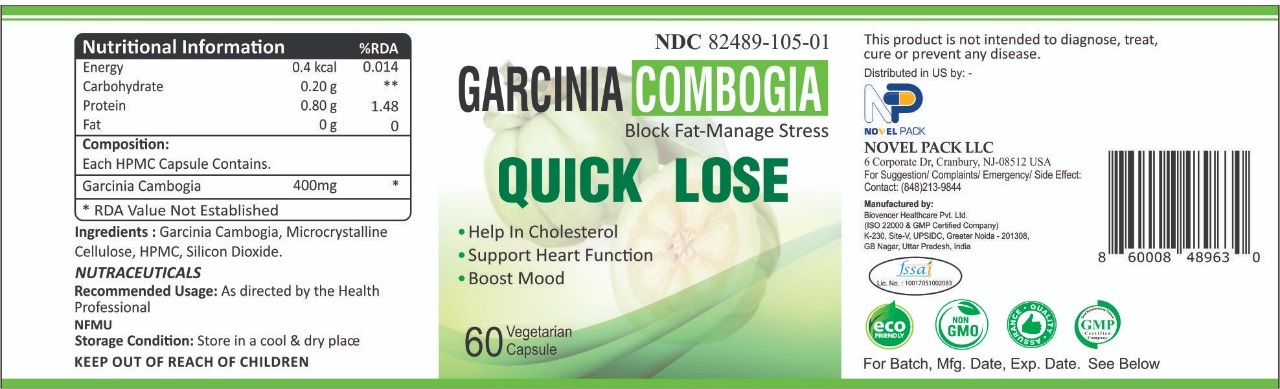 DRUG LABEL: Quick Lose
NDC: 82489-105 | Form: CAPSULE
Manufacturer: NOVEL PACK LLC
Category: other | Type: DIETARY SUPPLEMENT
Date: 20220502

ACTIVE INGREDIENTS: GARCINIA CAMBOGIA FRUIT 400 mg/1 1
INACTIVE INGREDIENTS: MICROCRYSTALLINE CELLULOSE; HYDROXYPROPYL CELLULOSE, UNSPECIFIED; SILICON DIOXIDE

QUICK LOSE
Garcinia Combogia

STATEMENT OF IDENTITY

Quick Lose

Garcini Combogia

Bloc Fat-Manage Stress

Storage Condition

Store in a cool and dry place.

KEEP OUT OF REACH OF CHILDREN

Recommended Usage

As directed by Health professional